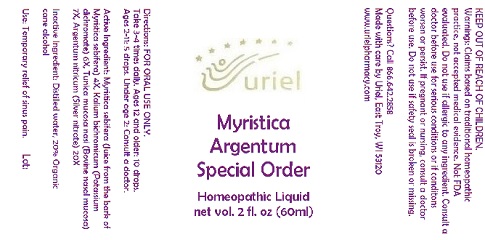 DRUG LABEL: Myristica Argentum Special Order
NDC: 48951-7144 | Form: LIQUID
Manufacturer: Uriel Pharmacy Inc.
Category: homeopathic | Type: HUMAN OTC DRUG LABEL
Date: 20180427

ACTIVE INGREDIENTS: VIROLA SEBIFERA RESIN 4 [hp_X]/1 mL; DICHROMATE ION 6 [hp_X]/1 mL; BOS TAURUS NASAL MUCOSA 7 [hp_X]/1 mL; SILVER 20 [hp_X]/1 mL
INACTIVE INGREDIENTS: WATER; ALCOHOL

Myristica Argentum Special Order

INDICATIONS AND USAGE

Directions: FOR ORAL USE ONLY.

DOSAGE AND ADMINISTRATION

Take 3-4 times daily. Ages 12 and older: 10 drops. Ages 2-11: 5 drops. Under age 2: Consult a doctor.

Active Ingredient: Myristica sebifera (Juice from the bark of Myristica sebifera) 4X, Kalium bichromicum (Potassium dichromate) 6X, Tunica mucosa nasi (Bovine nasal mucosa) 7X, Argentum nitricum (Silver nitrate) 20X

Inactive Ingredient: Distilled water, 20% Organic cane alcohol

PURPOSE

Use: Temporary relief of sinus pain.

KEEP OUT OF REACH OF CHILDREN.

WARNINGS

Warnings: Claims based on traditional homeopathic practice, not accepted medical evidence. Not FDA evaluated. Do not use if allergic to any ingredient. Consult a doctor before use for serious conditions or if conditons worsen or persist. If pregnant or nursing, consult a doctor before use. Do not use if safety seal is broken or missing.

QUESTIONS

Questions? Call 866.642.2858 Made with care by Uriel, East Troy, WI 53120 www.urielpharmacy.com